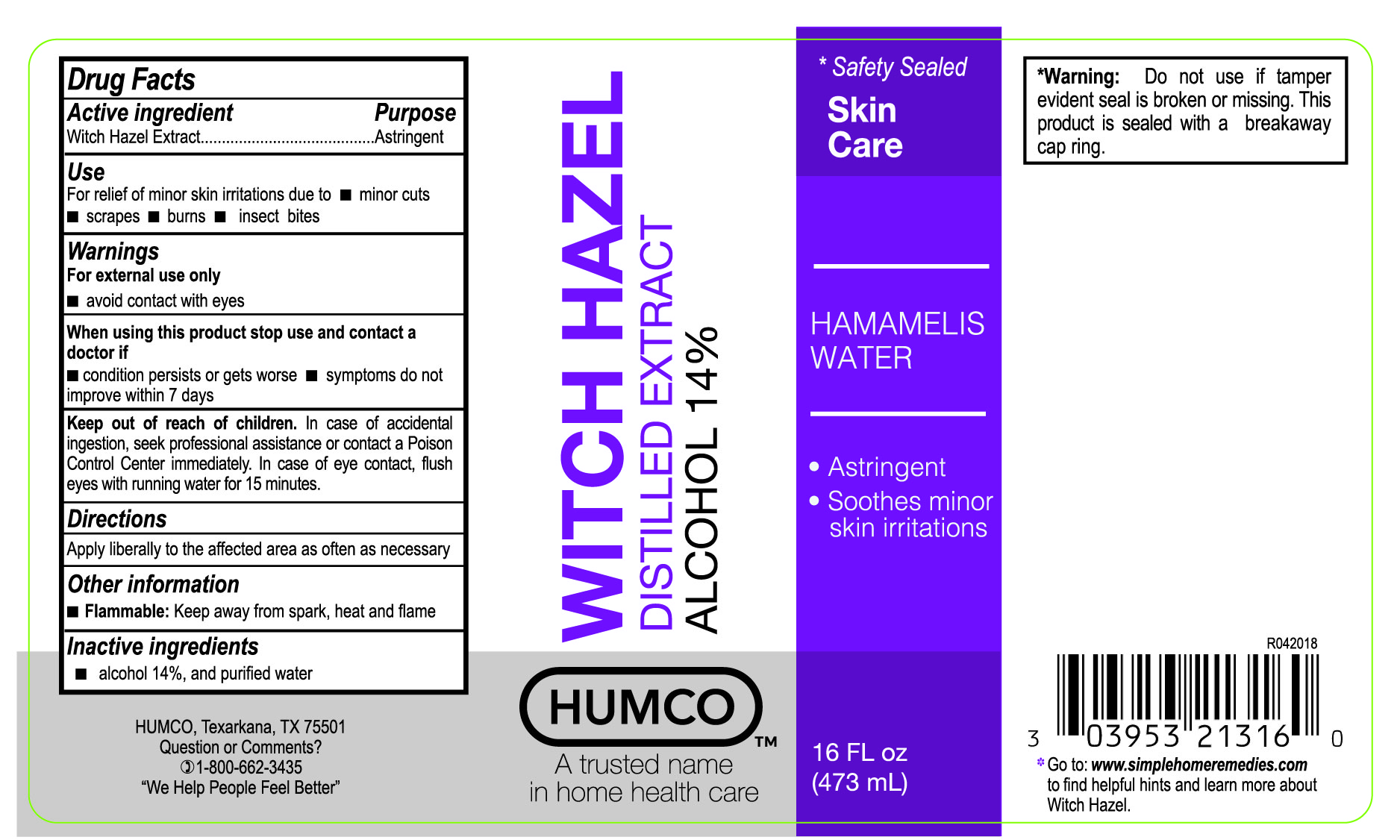 DRUG LABEL: Humco Witch Hazel
NDC: 0395-3213 | Form: LIQUID
Manufacturer: Humco Holding Group, Inc.
Category: otc | Type: HUMAN OTC DRUG LABEL
Date: 20231215

ACTIVE INGREDIENTS: WITCH HAZEL 884 mg/1 mL
INACTIVE INGREDIENTS: ALCOHOL; WATER

Humco Witch Hazel

Drug Facts

Active Ingredient

Wicth Hazel

Purpose

Astringent

Use

For relief of minor skin irritations due to:

- Minor cuts
- scrapes
- burns
- insect bites

Warnings

For external use only.

- avoid contact with eyes.

When using this product stop use and consult a doctor if:

- condition persists or gets worse.
- symptoms do not improve in 7 days.

Keep out of reach of children.

In case of accidental ingestion, seek professional assistance or contact a Poison Control Center immediately. In case of eye contact, flush eyes with running water for 15 minutes.

Directions

Apply liberally to the affected area as often as necessary.

Inactive ingredents

Alcohol 14% and purified water.